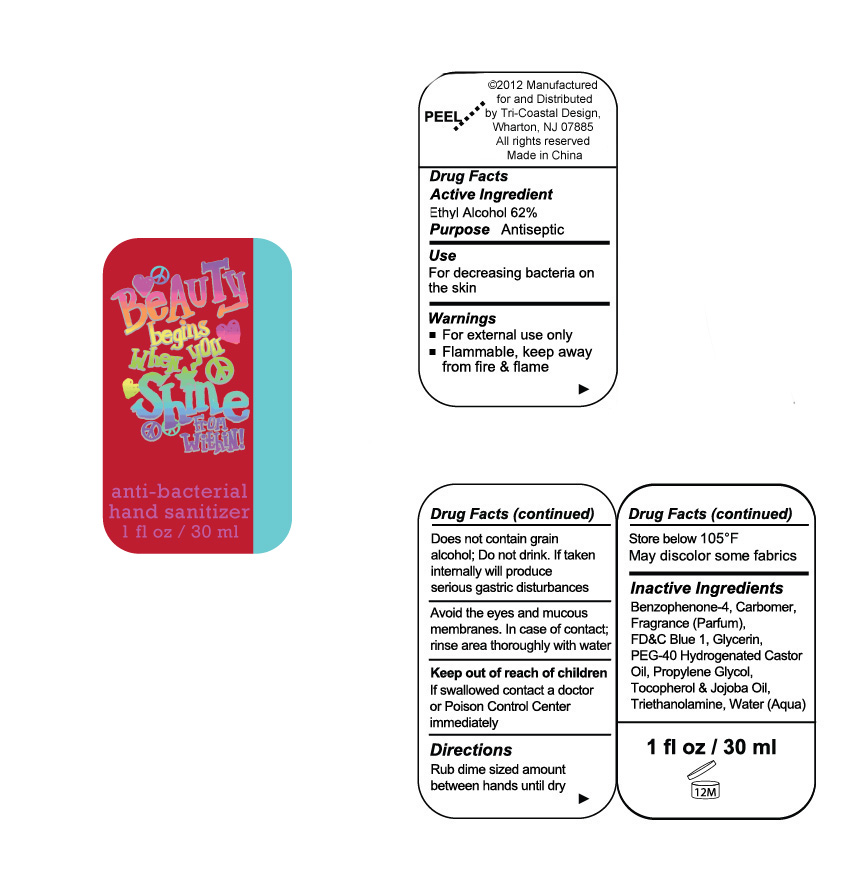 DRUG LABEL: anti bacterial hand sanitizer
NDC: 49852-012 | Form: LIQUID
Manufacturer: Tri-Coastal Design Company Inc.
Category: otc | Type: HUMAN OTC DRUG LABEL
Date: 20181228

ACTIVE INGREDIENTS: ALCOHOL 62 mL/100 mL
INACTIVE INGREDIENTS: SULISOBENZONE; FD&C BLUE NO. 1; GLYCERIN; POLYOXYL 40 HYDROGENATED CASTOR OIL; PROPYLENE GLYCOL; TOCOPHEROL; JOJOBA OIL; TROLAMINE; WATER

Drug Facts

Active Ingredient

Ethyl Alcohol 62%

Purpose

Antiseptic

Uses

• For handwashing to decrease bacteria on the skin

Warnings

• For external use only

• Flammable, keep away from fire and flame

Does not contain grain alcohol. Do not drink. If taken internally will produce serious gastric disturbances

Avoid eyes and mucous membranes

In case of contact, rinse area throoughly with water

Keep out of reach of children

If swallowed contact a doctor or Poison Control Center immediately

Directions

Rub dime sized amount between hands until dry

Other information

Store below 105°F

May discolor some fabrics

Inactive Ingredients

Benzophenone-4, Carbomer, Fragrance, FD&C Blue 1, Glycerin, PEG-40 Hydrogenated Castor Oil, Propylene Glycol, Tocopherol, Jojoba Oil, Triethanolamine, Water(Aqua)